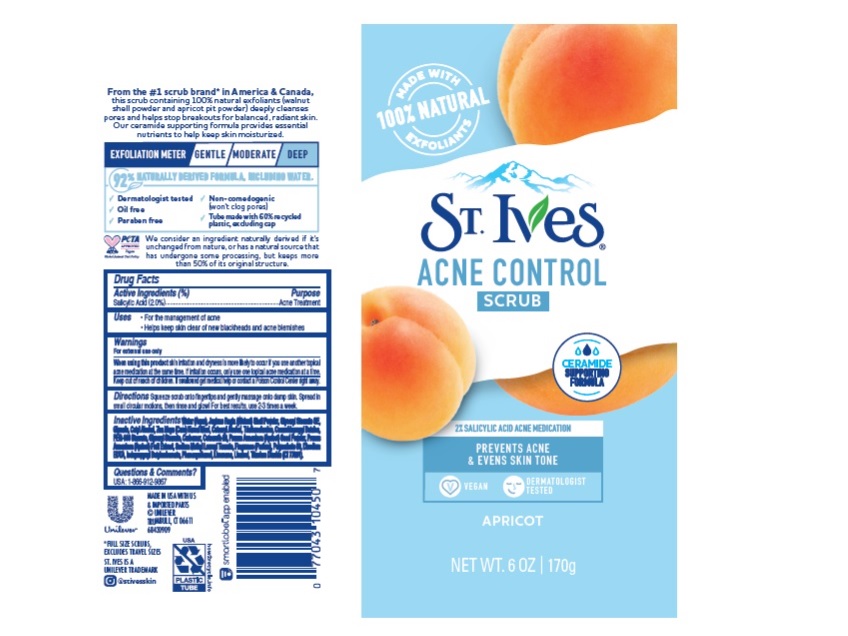 DRUG LABEL: St. Ives
NDC: 64942-2081 | Form: LOTION
Manufacturer: CONOPCO Inc. d/b/a Unilever
Category: otc | Type: HUMAN OTC DRUG LABEL
Date: 20241025

ACTIVE INGREDIENTS: SALICYLIC ACID 0.02 g/1 g
INACTIVE INGREDIENTS: SODIUM LAUROYL METHYL TAURATE; LIMONENE, (+)-; GLYCERYL STEARATE SE; WATER; CETOSTEARYL ALCOHOL; CORN GRAIN; CETYL ALCOHOL; TROLAMINE; COCAMIDOPROPYL BETAINE; PEG-100 STEARATE; GLYCERYL MONOSTEARATE; IODOPROPYNYL BUTYLCARBAMATE; PHENOXYETHANOL; TITANIUM DIOXIDE; CARBOMER HOMOPOLYMER, UNSPECIFIED TYPE; POLYSORBATE 60; EDETATE DISODIUM ANHYDROUS; GLYCERIN; APRICOT; PRUNUS ARMENIACA SEED; JUGLANS REGIA SHELL; LINALOOL, (+/-)-

St. Ives Acne Control Apricot Scrub

Active ingredient

Salicylic Acid (2%)

Purpose

Acne Treatment

Uses

For the managemnet of acne
Helps keep skin clear of new blackheads and acne blemishes

Warnings

For external use only

When using this product skin irritation and dryness is more likely to occur if you use another topical acne medication at the same time. If irritation occues, only use one topical acne medication at a time.

Keep out of reach of children
If swallowed, get medical help or contact a Poison Control Center right away.

Directions

Squeeze scrub onto fingertips and gently massage onto damp skin. Spread in small circular motions, then rinse and glow! For best results, use 2-3 times a week

Inactive ingredients

Water (Aqua), Juglans Regia (Walnut) Shell Powder, Glyceryl Stearate SE, Glycerin, Cetyl Alcohol, Zea Mays (Corn) Kernel Meal, Cetearyl Alcohol, Triethanolamine, Cocamidopropyl Betaine, PEG-100 Stearate, Glyceryl Stearate, Carbomer, Ceteareth-20, Prunus Armeniaca (Apricot) Seed Powder, Prunus Armeniaca (Apricot) Fruit Extract, Sodium Methyl Lauroyl Taurate, Fragrance (Parfum), Polysorbate 60, Disodium EDTA, Iodopropynyl Butylcarbamate, Phenoxyethanol, Limonene, Linalool, Titanium Dioxide (CI 77891).

Questions or comments?

USA: 1-866-912-9867